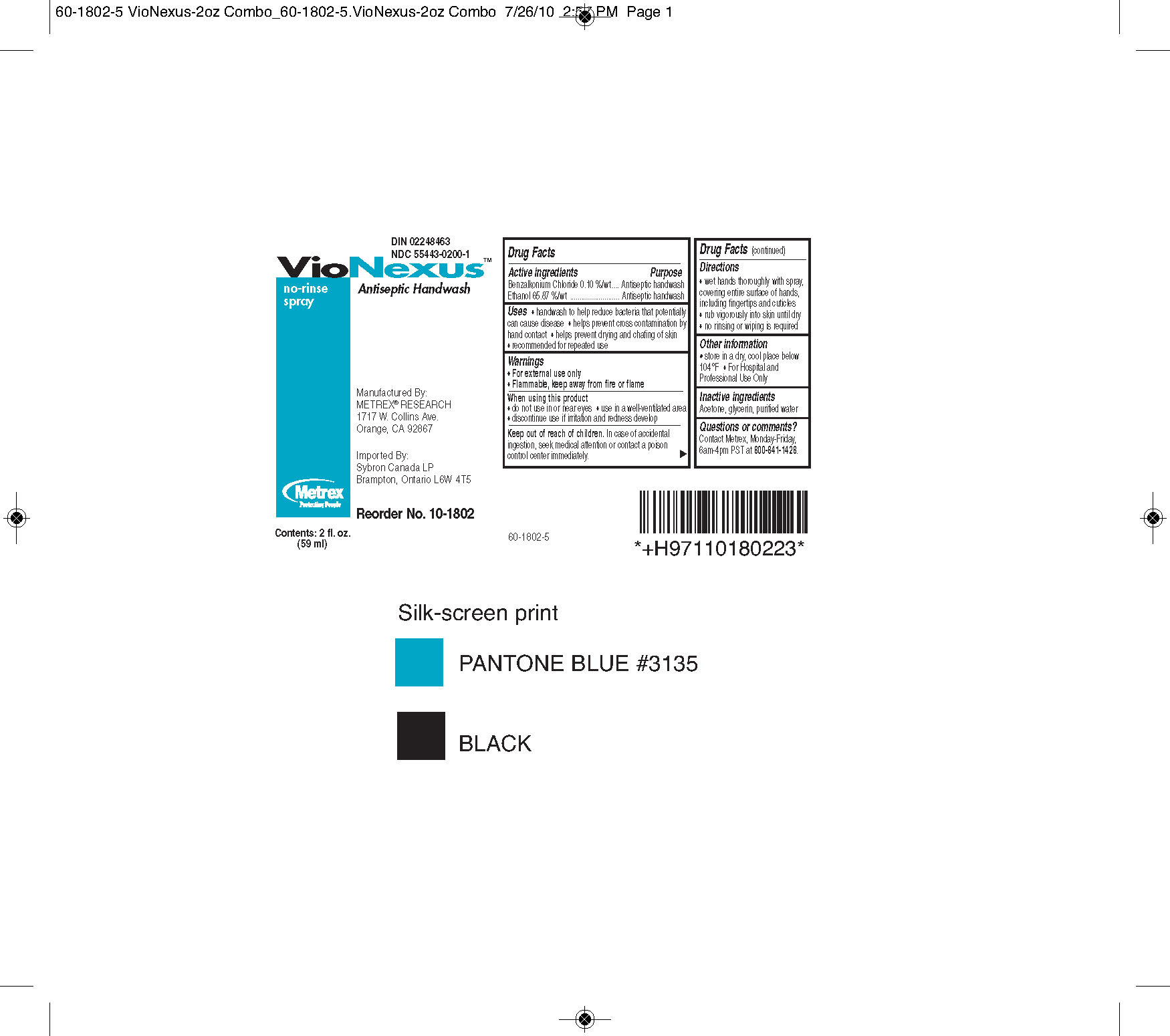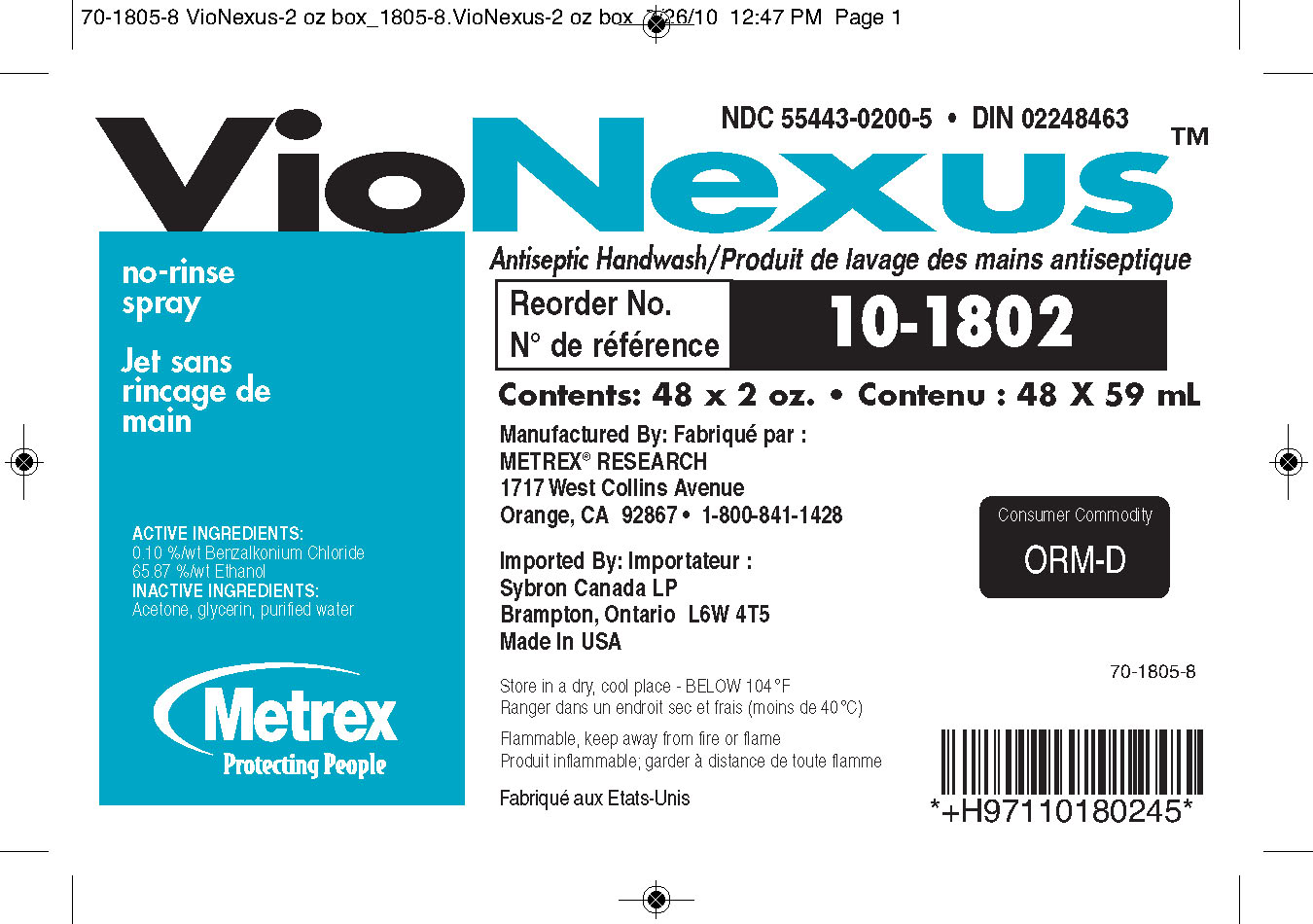 DRUG LABEL: VioNexus
NDC: 55443-0200 | Form: LIQUID
Manufacturer: Metrex Research
Category: otc | Type: HUMAN OTC DRUG LABEL
Date: 20100830

ACTIVE INGREDIENTS: BENZALKONIUM CHLORIDE 0.085 g/100 mL; ETHANOL 77.01 g/100 mL

VioNexus No Rinse Spray

Principal Display Panel

VioNexus
no-rinse spray
Antiseptic Handwash
Metrex
Protecting People
MADE IN USA
Contents:
x Liter
x fl. oz.
x mL
Manufactured By:
METREX RESEARCH CORPORATION
1717 W. Collins Avenue
Orange, CA 92867
Imported By:
Sybron Canada LP
Brampton, Ontario L6W 4T5

Drug Facts

Active ingredients Purpose
Benzalkonium Chloride 0.10%/wt .......................Antiseptic handwash
Ethanol 65.87%/wt ............................................Antiseptic handwash

Uses

- for handwashing to decrease bacteria on the skin
- helps prevent cross contamination by hand contact
- helps prevent drying and chafing of skin
- recommended for repeated use

Warnings

- For external use only
- Flammable, keep away from fire or flame

When using this product

- do not use in or near eyes
- use in a well-ventilated area
- discontinue use if irritation and redness develop

Keep out of reach of children

In case of accidental ingestion, seek medical attention or contact a poison control center immediately.

Directions

- wet hands thoroughly with spray, covering entire surface of hands, including fingertips and cuticles
- rub vigorously into skin until dry
- no rinsing or wiping is required

Other information

- store in a dry, cool place below 104 F
- recommended for use in the VioNexus No-Touch Dispenser
- for hospital and professional use only

Inactive Ingredients

Acetone, glycerin, purified water

Questions or comments?

For product or technical information, contact Metrex, Monday-Friday, 6am-4pm PST at 800-841-1428 or visit our website at www.metrex.com.

PACKAGE LABEL

image of VioNexusNRSBottle
image of VioNexusNRSBox